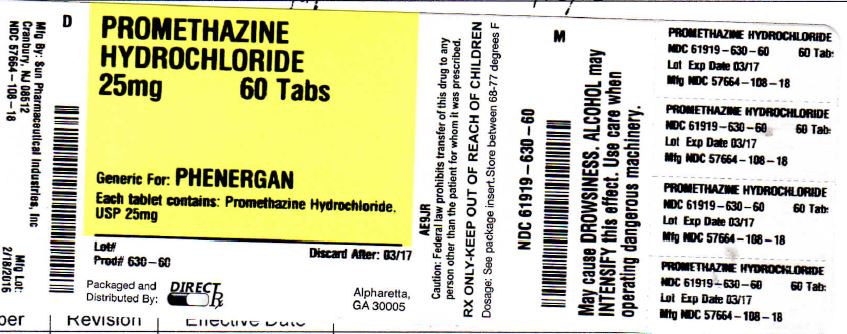 DRUG LABEL: PROMETHAZINE HYDROCHLORIDE
NDC: 61919-630 | Form: TABLET
Manufacturer: DIRECT RX
Category: prescription | Type: HUMAN PRESCRIPTION DRUG LABEL
Date: 20160222

ACTIVE INGREDIENTS: PROMETHAZINE HYDROCHLORIDE 25 mg/1 1
INACTIVE INGREDIENTS: HYPROMELLOSES; LACTOSE MONOHYDRATE; CELLULOSE, MICROCRYSTALLINE; MAGNESIUM STEARATE

PROMETHAZINE HYDROCHLORIDE 25mg